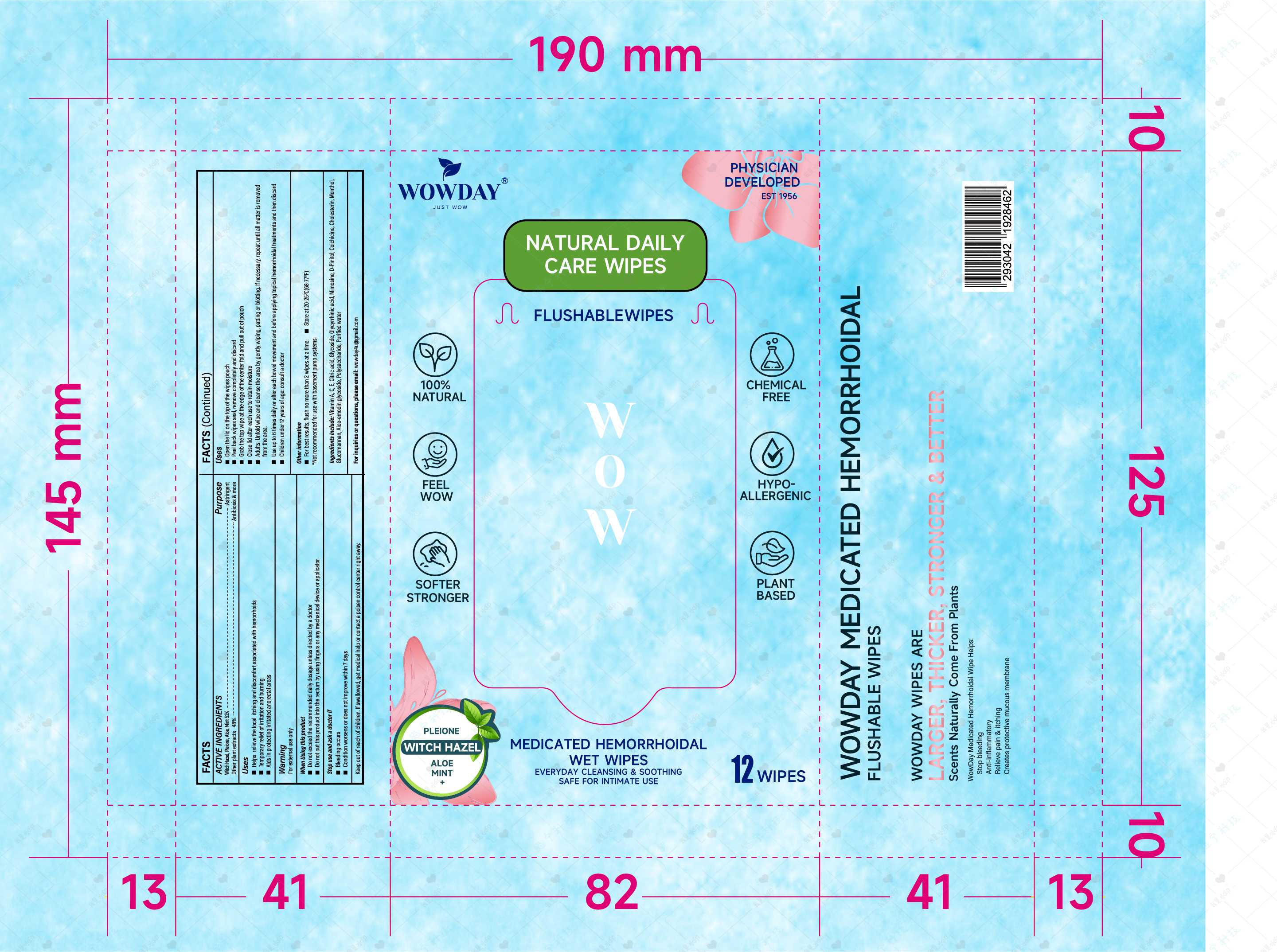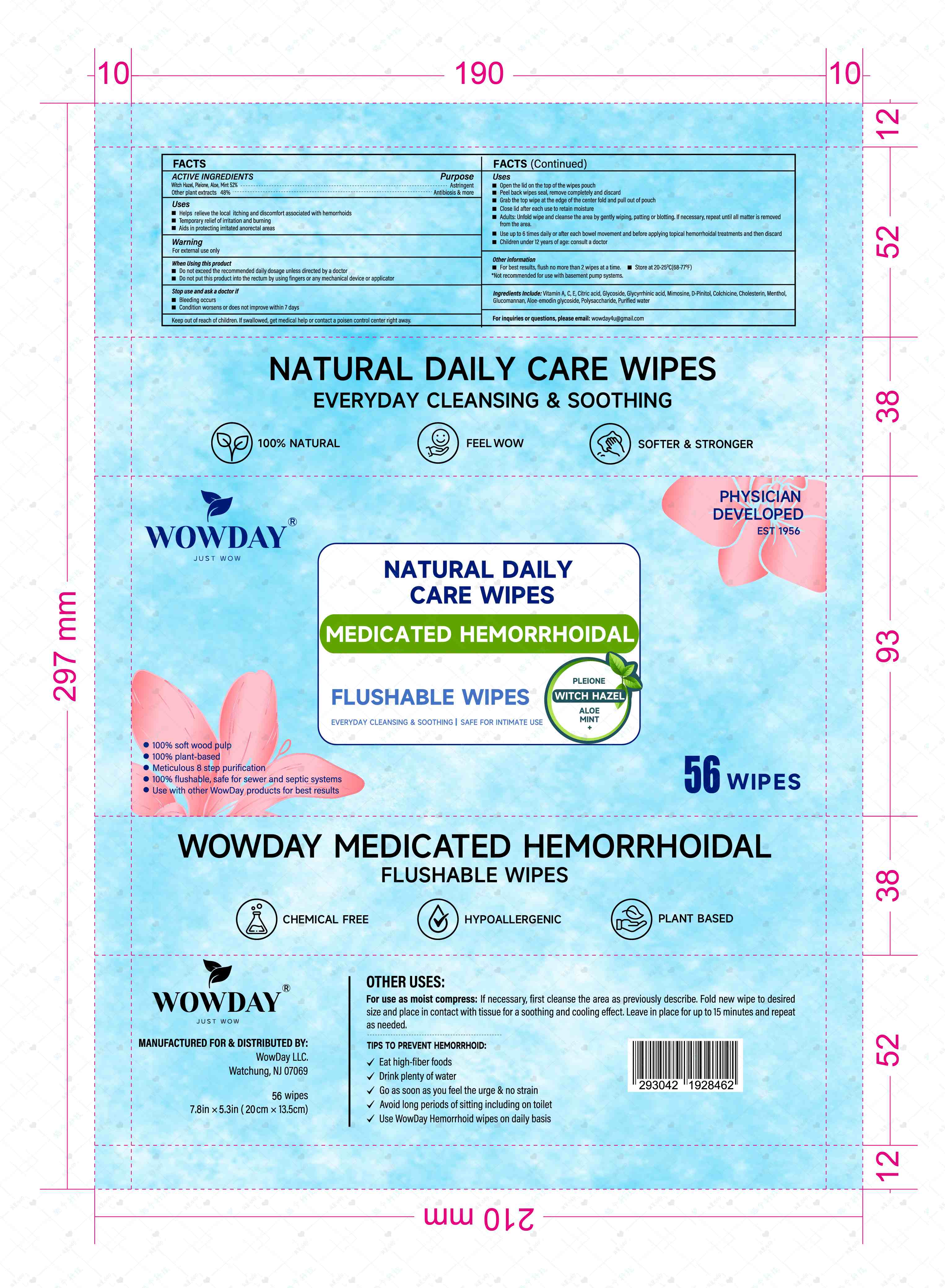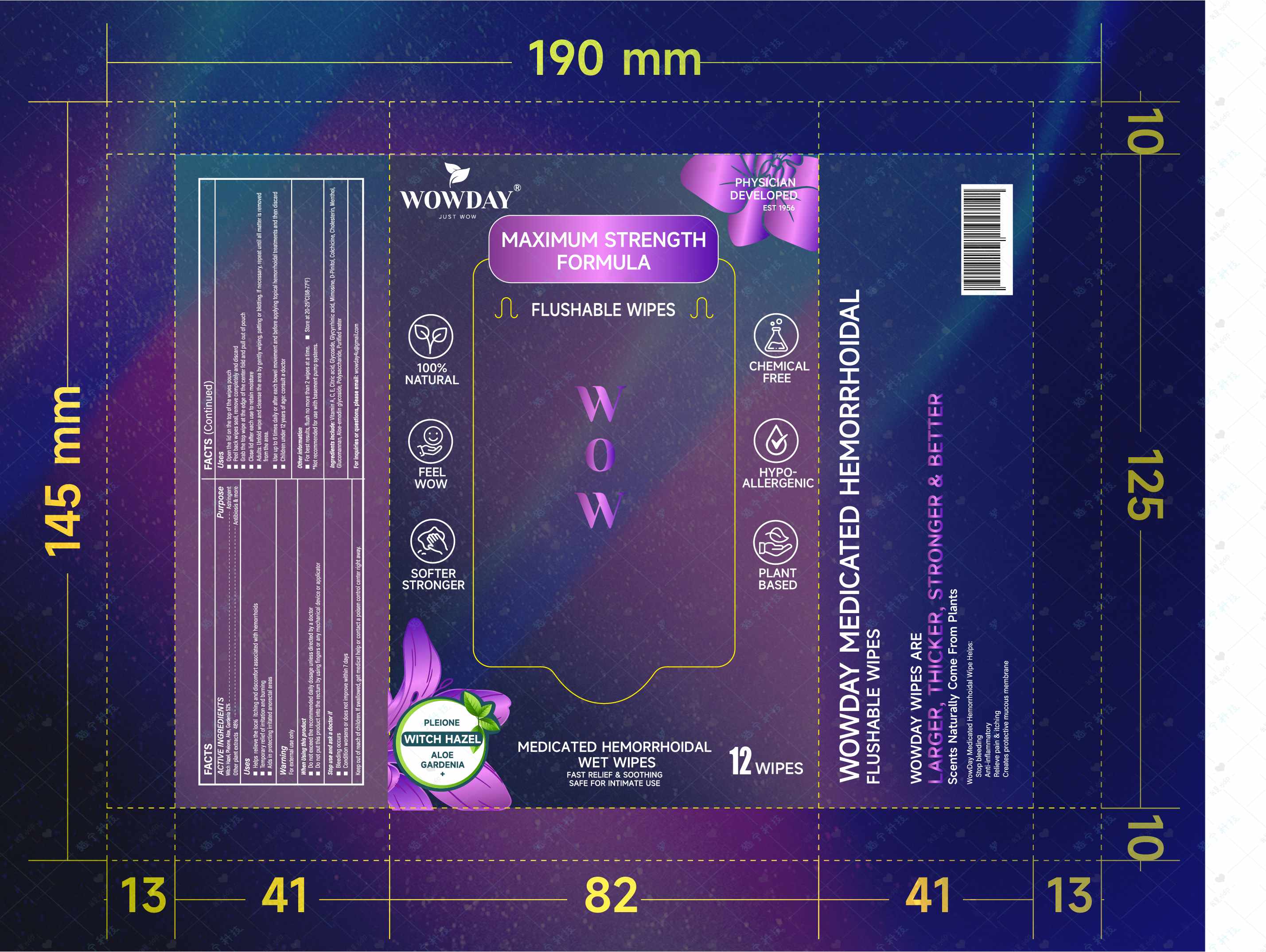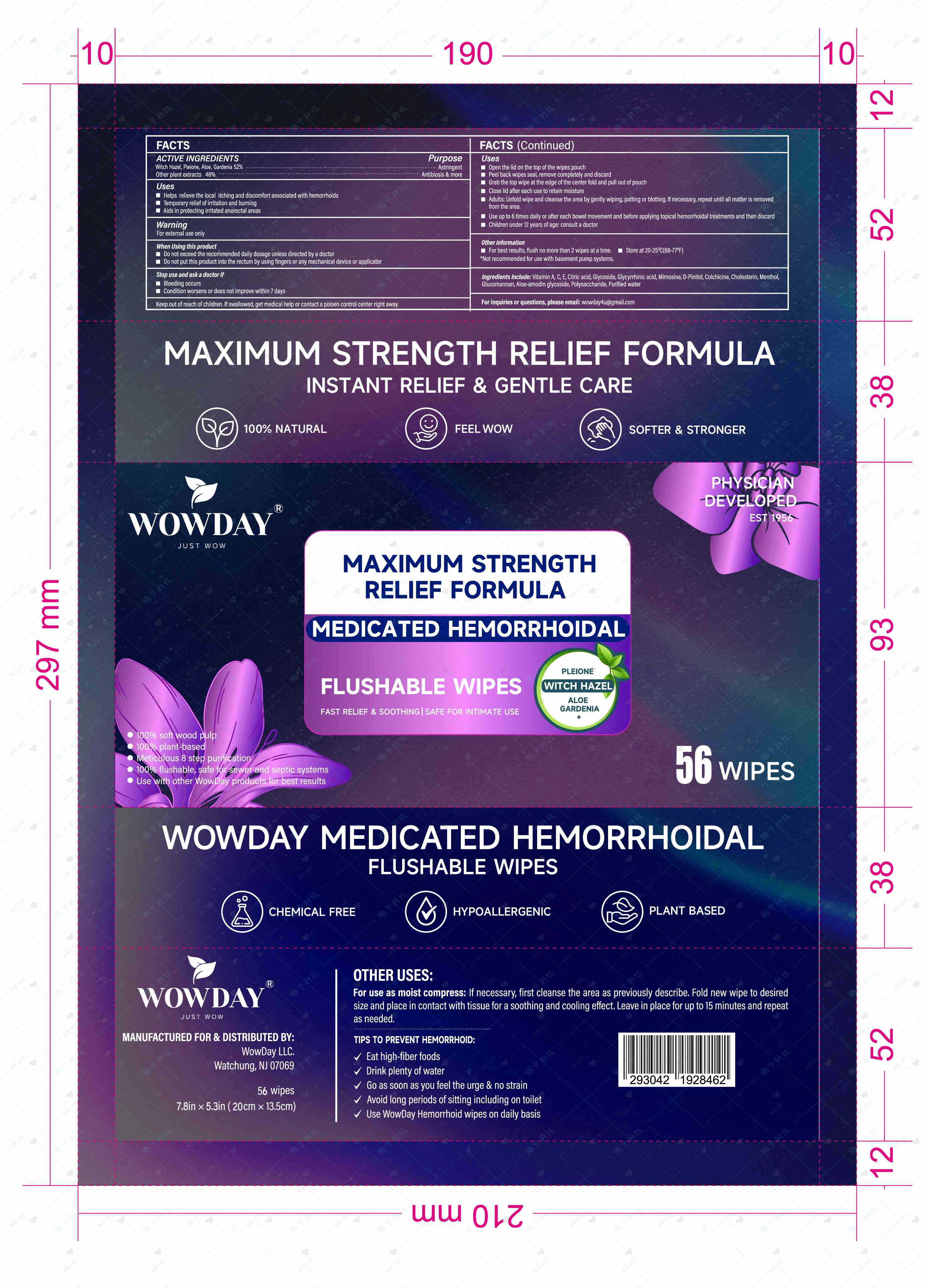 DRUG LABEL: WOWDAY MEDICATED HEMORRHOIDAL FLUSHABLE WIPES
NDC: 85511-001 | Form: PATCH
Manufacturer: Shanghai Tongjie Commodity Co.,Ltd.
Category: otc | Type: HUMAN OTC DRUG LABEL
Date: 20250409

ACTIVE INGREDIENTS: WITCH HAZEL 20 mg/100 mg; MINT 8 mg/100 mg; ALOE 10 mg/100 mg; PLEIONE YUNNANENSIS WHOLE 20 mg/100 mg
INACTIVE INGREDIENTS: XANTHAN GUM; MIMOSINE; MENTHOL; CITRIC ACID; REBAUDIOSIDE A; CHOLESTERYL NONANOATE; GLUCOMANNAN; VITAMIN E POLYETHYLENE GLYCOL SUCCINATE; ASCORBIC ACID; VITAMIN A; COLCHICINE; ALOE EMODIN; WATER; PINITOL

ACTIVE INGREDIENT

Witch Hazel, Pleione, Aloe, Mint

PURPOSE

EVERYDAY CLEANSING & SOOTHINGI SAFE FOR INTIMATE USE

STOP USE

Bleeding occurs
Condition worsens or does not improve within 7 days

When Using this product
Do not exceed the recommended daily dosage unless directed by a doctorDo not put this product into the rectum by using fingers or any mechanical device or applicator

Keep out of reach of children. lf swallowed, get medical help or contact a poisen control center right away.

WARNINGS

For external use only

INDICATIONS AND USAGE

0pen the lid on the top of the wipes pouch
Peel back wipes seal, remove completely and discard
Grab the top wipe at the edge of the center fold and pull out of pouch
Close lid after each use to retain moisture
Adults: Unfold wipe and cleanse the area by gently wiping, pating or blotting. lf necessary, repeat until all matter is removed
from the area.Use up to 6 times daily or after each bowel movement and before applying topical hemorrhoidal treatments and then discardChildren under 12 years of age: consult a doctor

DOSAGE AND ADMINISTRATION

Adults: Unfold wipe and cleanse the area by gently wiping, pating or blotting. lf necessary, repeat unti all matter is removed
from the area.
I Use up to 6 times daily or after each bowel movement and before applying topical hemorrhoidal treatments and then discard

INACTIVE INGREDIENT

Vitamin A
Vitamin C
Vitamin E
Glycyrrhizic acid
Mimosine
D-Pinitol
Colchicine
Aloe-emodin glycoside
Polysaccharide
Citric acid
Glycoside
Cholesterin
Menthol
Glucomannan
Purified water